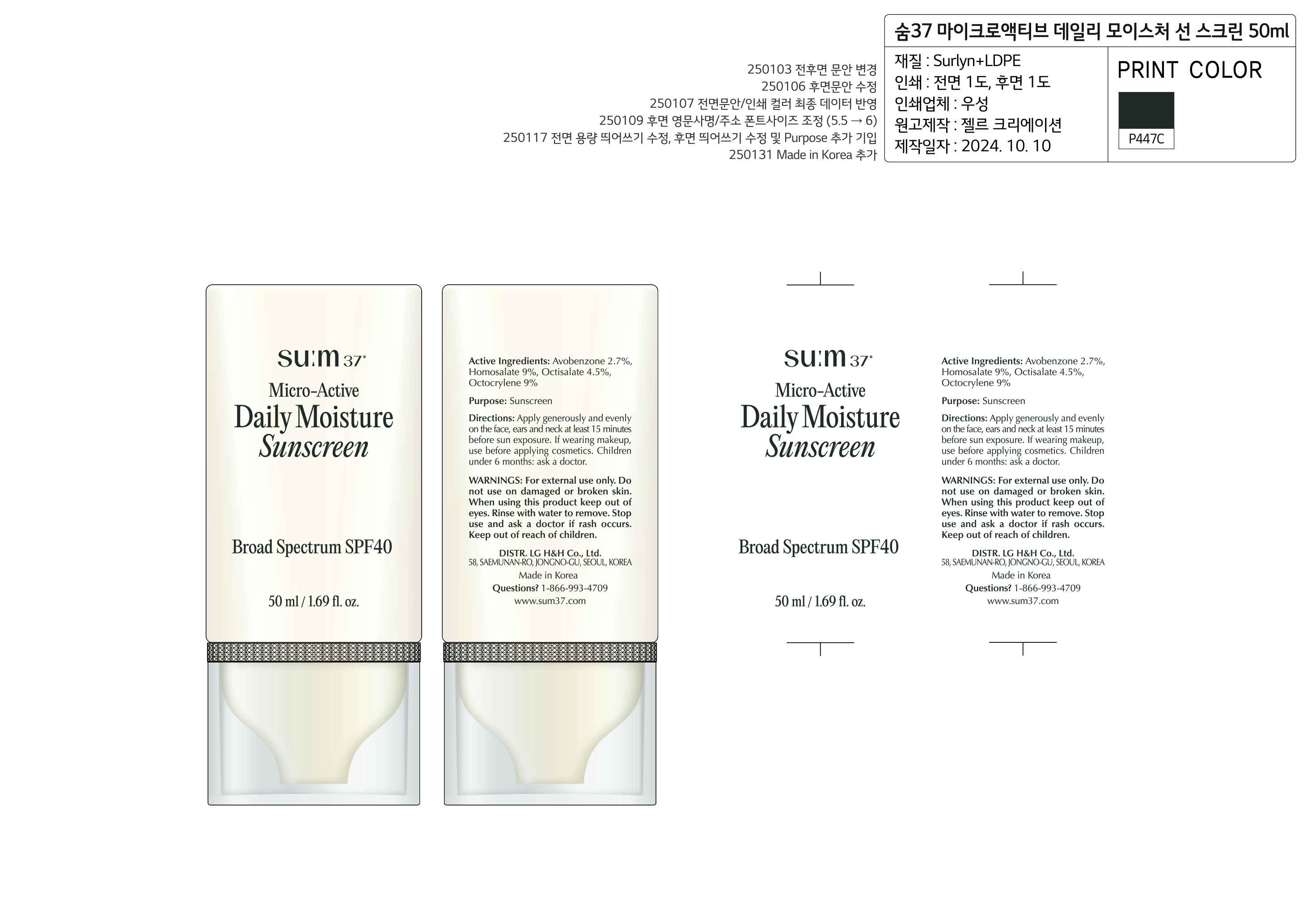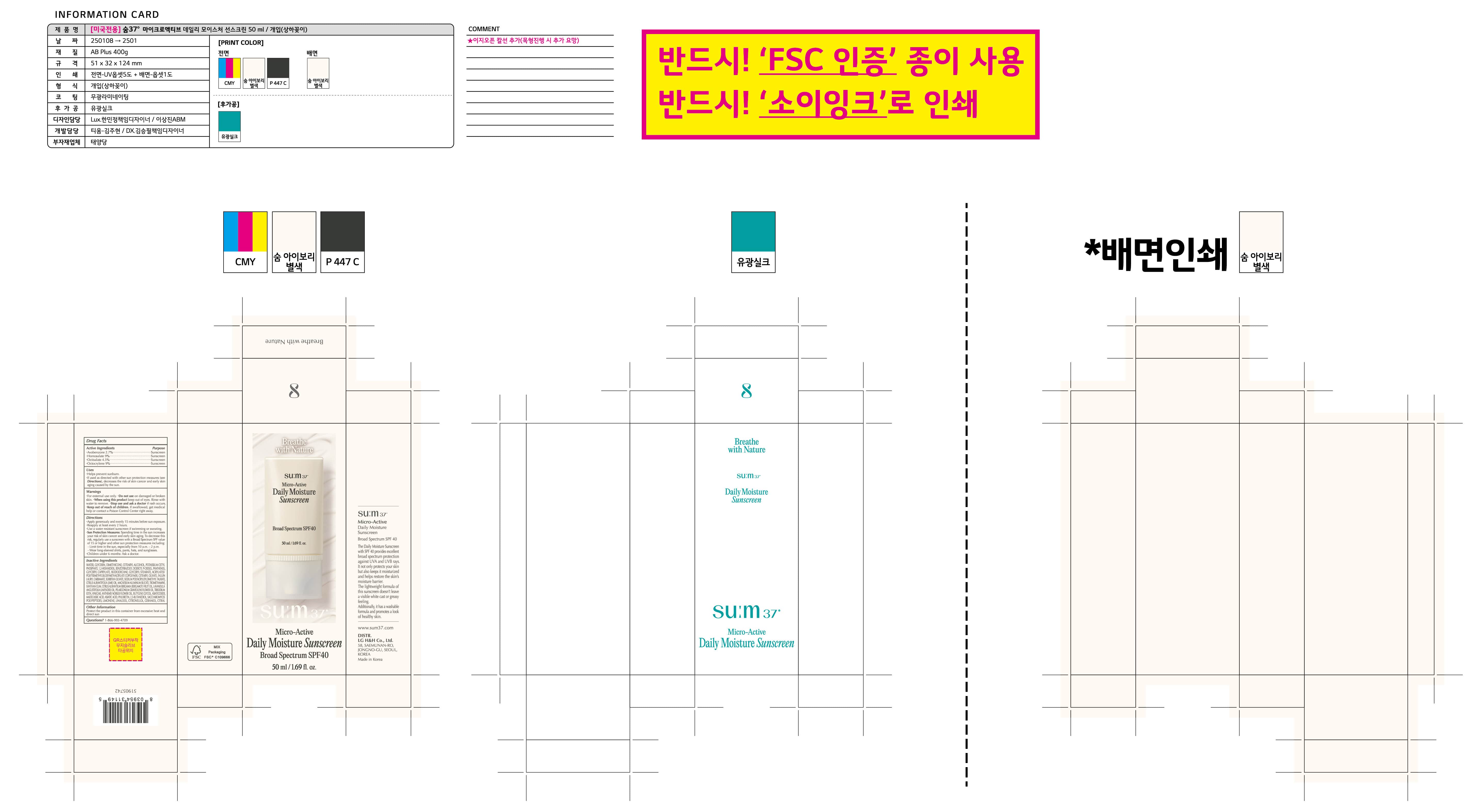 DRUG LABEL: Sum 37 Micro Active Daily Moisture Sunscreen
NDC: 53208-440 | Form: CREAM
Manufacturer: LG HOUSEHOLD & HEALTH CARE LTD.
Category: otc | Type: HUMAN OTC DRUG LABEL
Date: 20250303

ACTIVE INGREDIENTS: OCTISALATE 45 mg/1 mL; OCTOCRYLENE 90 mg/1 mL; AVOBENZONE 27 mg/1 mL; HOMOSALATE 90 mg/1 mL
INACTIVE INGREDIENTS: TRISODIUM EDTA; CITRUS AURANTIUM BERGAMIA (BERGAMOT) FRUIT OIL; LAVANDULA ANGUSTIFOLIA (LAVENDER) OIL; PELARGONIUM GRAVEOLENS FLOWER OIL; PANTHENOL; ISODODECANE; GLYCERYL STEARATE; CETEARYL OLIVATE; ASIATICOSIDE; BENZOTRIAZOLYL DODECYL P-CRESOL; GLYCERYL CAPRYLATE; SODIUM POLYACRYLOYLDIMETHYL TAURATE; CITRUS AURANTIFOLIA (LIME) OIL; PHLORETIN; GERANIOL; CITRONELLOL; CITRAL; POTASSIUM CETYL PHOSPHATE; ACETIC ACID; ANTHEMIS NOBILIS FLOWER OIL; GLYCERIN; TROMETHAMINE; XANTHAN GUM; INULIN LAURYL CARBAMATE; SORBITAN OLIVATE; DIMETHICONE; MAGNESIUM ALUMINUM SILICATE; LIMONENE, (+)-; BUTYL ACRYLATE/METHYL METHACRYLATE/TRIMETHYLSILOXYMETHACRYLATE COPOLYMER; 1,2-HEXANEDIOL; CETEARYL ALCOHOL; LINALOOL; BUTYLENE GLYCOL; MADECASSIC ACID; 2,3-BUTANEDIOL; ASIATIC ACID; WATER

Active Ingredients

Avobenzone 2.7%
Homosalate 9%
Octisalate 4.5%
Octocrylene 9%

Purpose

Sunscreen

Uses

Helps prevent sunburn.
If used as directed with other sun protection measures (see Directions), decreases the risk of skin cancer and early skin aging caused by the sun.

Warnings

For external use only

Do not use on damaged or broken skin.

When using this product keep out of eyes. Rinse with water to remove.

Stop use and ask a doctor if rash occurs.

Keep out of reach of children.

DOSAGE AND ADMINISTRATION

If swallowed, get medical help or contact a Poison Control Center right away.

Directions

Apply generously and evenly 15 minutes before sun exposure.
Reapply at least every 2 hours.
Use a water resistant sunscreen if swimming or sweating.
Sun Protection Measures: Spending time in the sun increases your risk of skin cancer and early skin aging. To decrease this risk, regularly use a sunscreen with a Broad Spectrum SPF value of 15 or higher and other sun protection measures including:
- Limit time in the sun, especially from 10 a.m. – 2 p.m.
- Wear long-sleeved shirts, pants, hats, and sunglasses.
Children under 6 months: Ask a doctor.

Inactive Ingredients

WATER, GLYCERIN, DIMETHICONE, CETEARYL ALCOHOL, POTASSIUM CETYL PHOSPHATE, 1,2-HEXANEDIOL, BENZOTRIAZOLYL DODECYL P-CRESOL, PANTHENOL, GLYCERYL CAPRYLATE, ISODODECANE, GLYCERYL STEARATE, ACRYLATES/POLYTRIMETHYLSILOXYMETHACRYLATE COPOLYMER, CETEARYL OLIVATE, INULIN LAURYL CARBAMATE, SORBITAN OLIVATE, SODIUM POLYACRYLOYLDIMETHYL TAURATE, CITRUS AURANTIFOLIA (LIME) OIL, MAGNESIUM ALUMINUM SILICATE, TROMETHAMINE, XANTHAN GUM, CITRUS AURANTIUM BERGAMIA (BERGAMOT) FRUIT OIL, LAVANDULA ANGUSTIFOLIA (LAVENDER) OIL, PELARGONIUM GRAVEOLENS FLOWER OIL, TRISODIUM EDTA, VINEGAR, ANTHEMIS NOBILIS FLOWER OIL, BUTYLENE GLYCOL, ASIATICOSIDE, MADECASSIC ACID, ASIATIC ACID, PHLORETIN, 2,3-BUTANEDIOL, SACCHAROMYCES POLYPEPTIDES, LIMONENE, LINALOOL, CITRONELLOL, GERANIOL, CITRAL.

Other Information

Protect the product in this container from excessive heat and direct sun

Questions?

1-866-993-4709